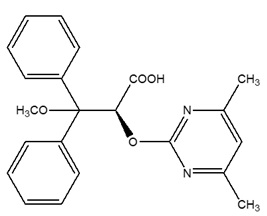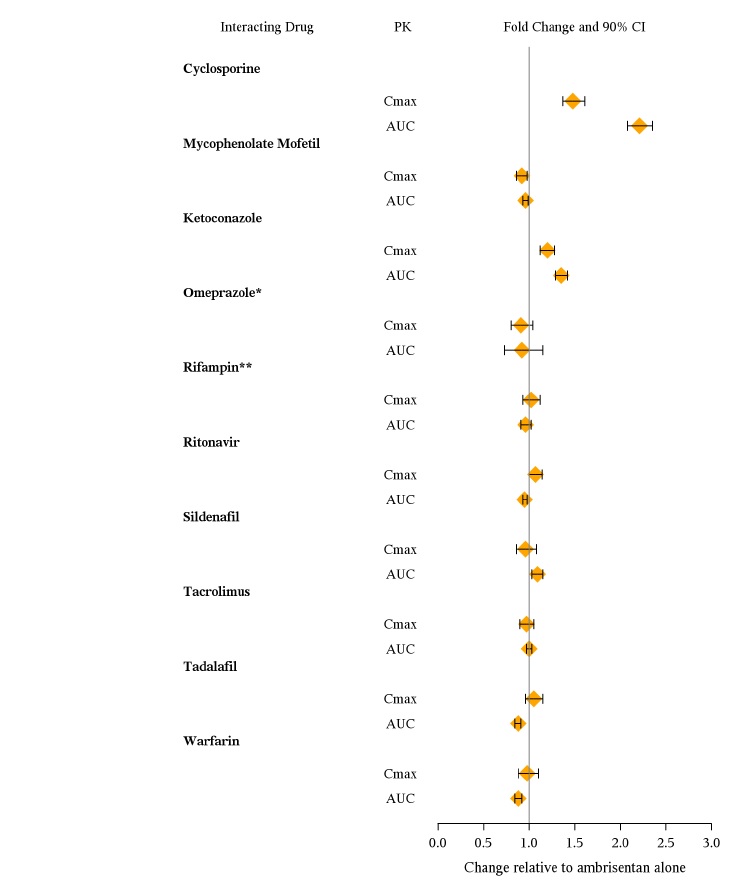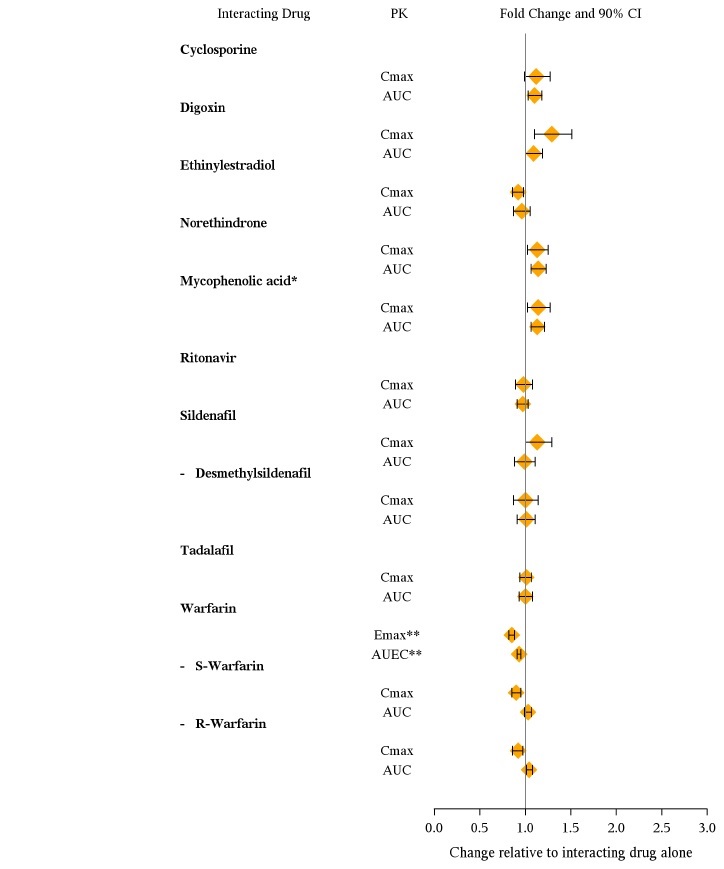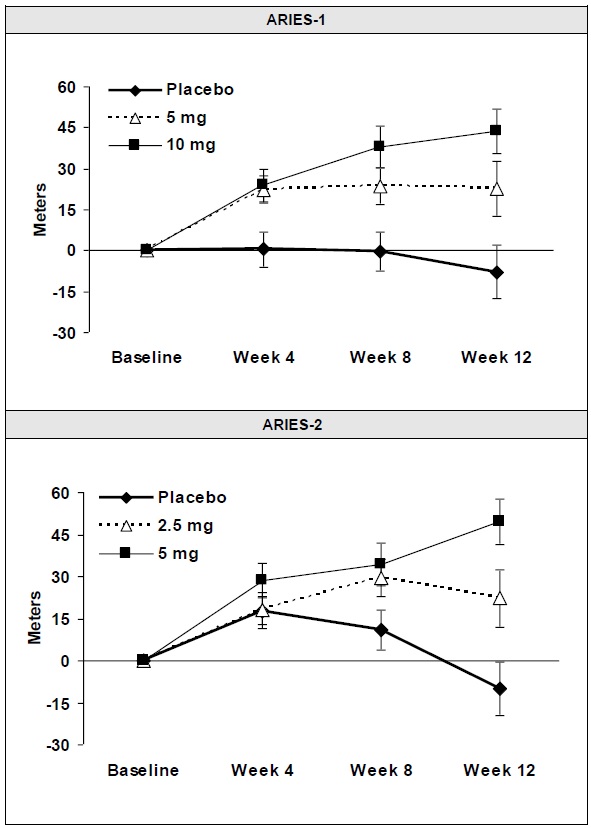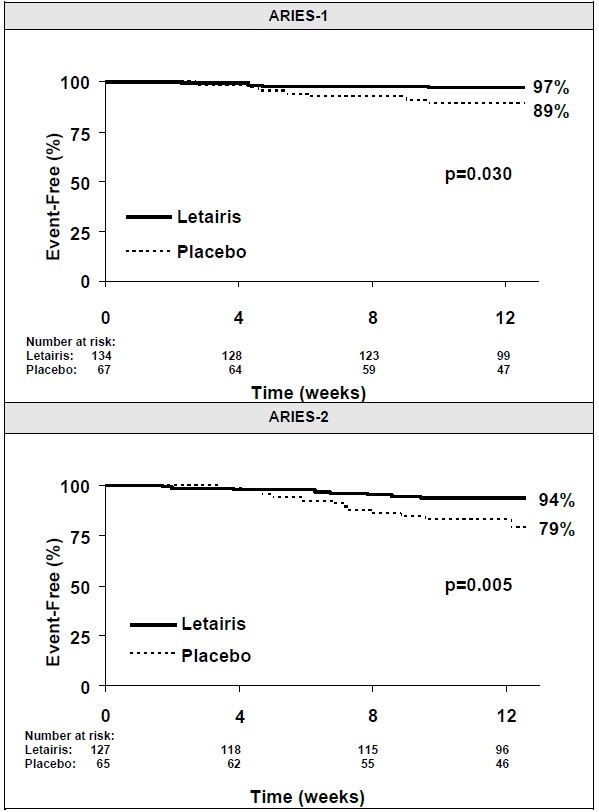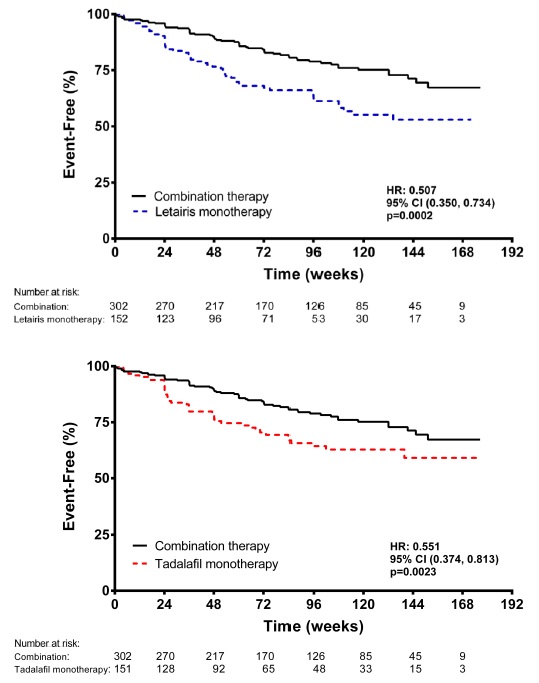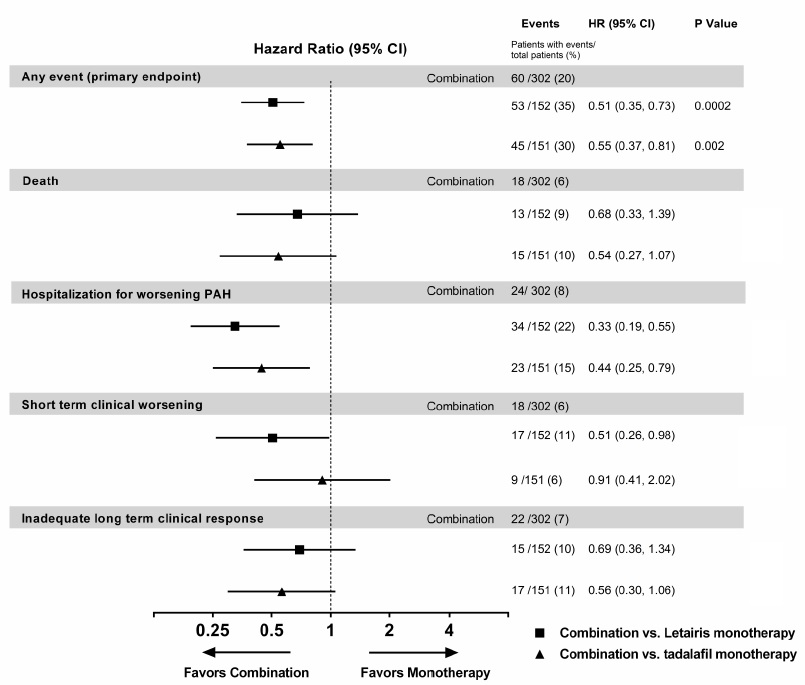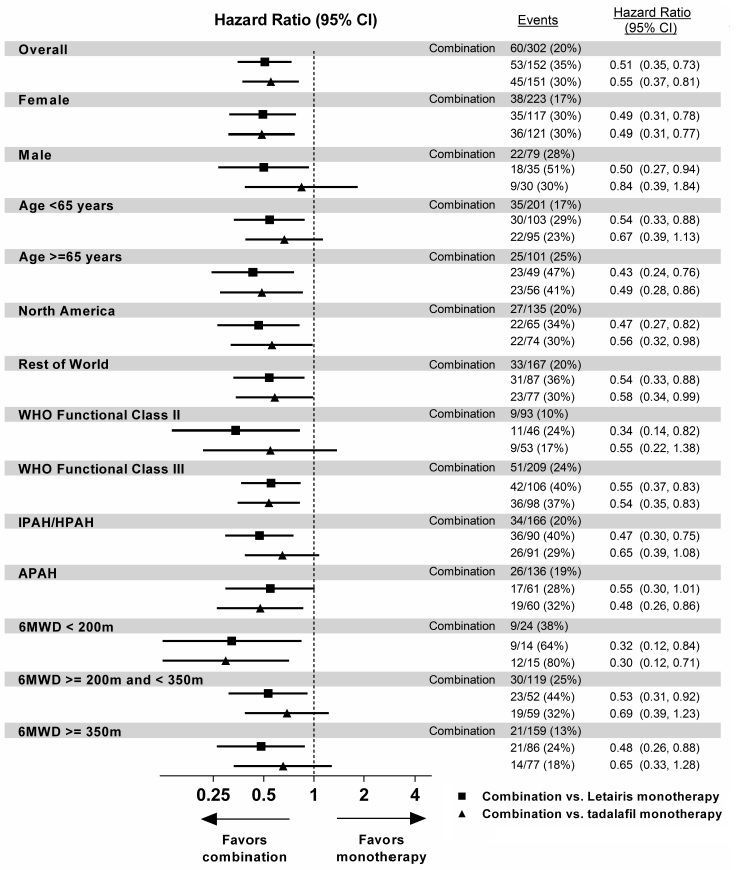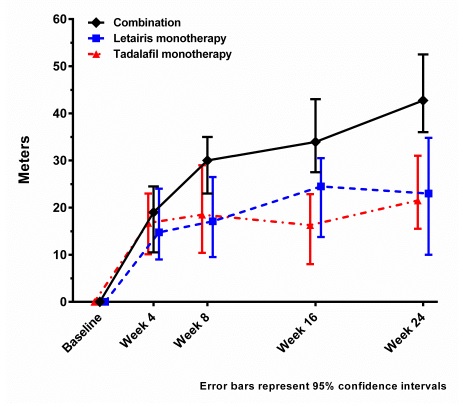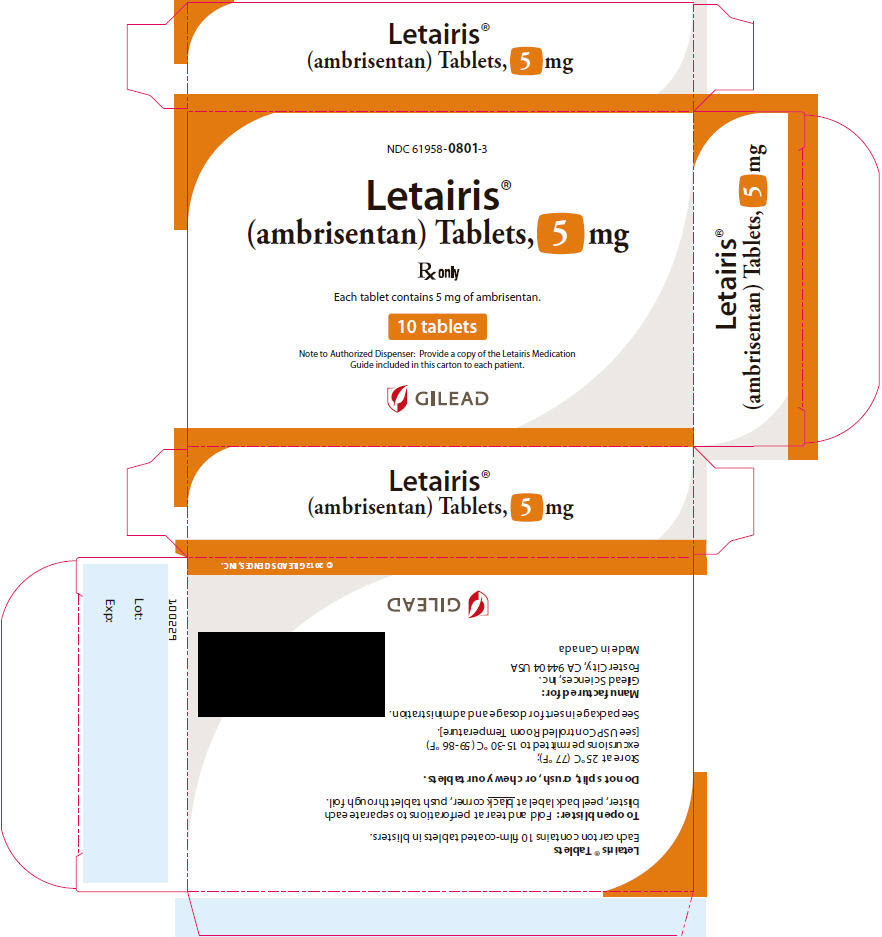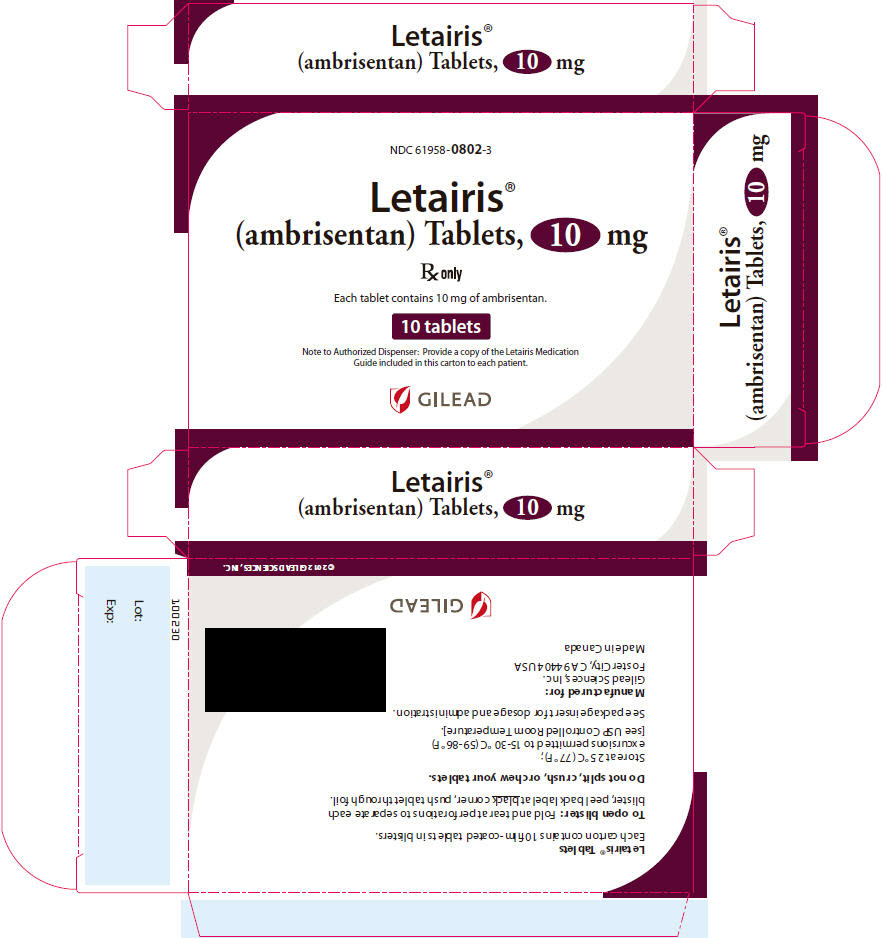 DRUG LABEL: Letairis
NDC: 61958-0801 | Form: TABLET, FILM COATED
Manufacturer: Gilead Sciences, Inc.
Category: prescription | Type: HUMAN PRESCRIPTION DRUG LABEL
Date: 20250822

ACTIVE INGREDIENTS: AMBRISENTAN 5 mg/1 1
INACTIVE INGREDIENTS: CROSCARMELLOSE SODIUM; LACTOSE MONOHYDRATE; MAGNESIUM STEARATE; MICROCRYSTALLINE CELLULOSE; FD&C RED NO. 40; ALUMINUM OXIDE; SOYBEAN LECITHIN; POLYETHYLENE GLYCOL 3350; POLYVINYL ALCOHOL, UNSPECIFIED; TALC; TITANIUM DIOXIDE

HIGHLIGHTS OF PRESCRIBING INFORMATION

These highlights do not include all the information needed to use LETAIRIS® safely and effectively. See full prescribing information for LETAIRIS.
Letairis (ambrisentan) tablets, for oral use
Initial U.S. Approval: 2007

WARNING: EMBRYO-FETAL TOXICITY

See full prescribing information for complete boxed warning.

- Based on animal data Letairis may cause fetal harm if used during pregnancy (4.1, 5.1, 8.1).
- Females of reproductive potential: Exclude pregnancy before the start of treatment. Use effective contraception prior to initiation of treatment, during treatment, and for one month after treatment with Letairis (2.2, 4.1, 5.1, 8.1, 8.3)
- When pregnancy is detected, discontinue Letairis as soon as possible (5.1).

RECENT MAJOR CHANGES

- Box Warning
- Indications and Usage (1)
- Dosage and Administration, Pregnancy Testing in
  Females of Reproductive Potential (2.2)
- Warnings and Precautions for Use
  Embryo-fetal Toxicity (5.1)
  Ambrisentan Risk Evaluation and Mitigation Strategy (REMS) (5.2)

04/2025
04/2025
04/2025
04/2025
(removed) 04/2025

1 INDICATIONS AND USAGE

Letairis is an endothelin receptor antagonist indicated for the treatment of pulmonary arterial hypertension (PAH) (WHO Group 1) in adult patients:

- To improve exercise ability and delay clinical worsening.
- In combination with tadalafil to reduce the risks of disease progression and hospitalization for worsening PAH, and to improve exercise ability.

Studies establishing effectiveness included trials predominantly in patients with WHO Functional Class II–III symptoms and etiologies of idiopathic or heritable PAH (60%) or PAH associated with connective tissue diseases (34%) (1).

2 DOSAGE AND ADMINISTRATION

- Initiate treatment at 5 mg once daily (2.1).
- May be started with tadalafil (2.1).
- Titrate at 4-week intervals as needed and tolerated (2.1).
- Do not split, crush, or chew tablets (2.1).

3 DOSAGE FORMS AND STRENGTHS

Tablet: 5 mg and 10 mg (3)

4 CONTRAINDICATIONS

- Pregnancy (4.1)
- Idiopathic Pulmonary Fibrosis (4.2)

5 WARNINGS AND PRECAUTIONS

- Fluid retention may require intervention (5.2).
- If patients develop acute pulmonary edema during initiation of therapy with Letairis, consider underlying pulmonary veno-occlusive disease and discontinue treatment if necessary (5.3).
- Decreases in sperm count have been observed in patients taking endothelin receptor antagonists (5.4).
- Decreases in hemoglobin have been observed within the first few weeks; measure hemoglobin at initiation, at 1 month, and periodically thereafter (5.5).

6 ADVERSE REACTIONS

- Most common adverse reactions (>3% compared to placebo) are peripheral edema, nasal congestion, sinusitis, and flushing (6.1).
- When used in combination with tadalafil, most common adverse reactions (>5% compared with either monotherapy) are peripheral edema, headache, nasal congestion, cough, anemia, dyspepsia, and bronchitis (6.1).

To report SUSPECTED ADVERSE REACTIONS, contact Gilead Sciences, Inc. at (1-800-445-3235, Option 3) or FDA at 1-800-FDA-1088 or www.fda.gov/medwatch.

7 DRUG INTERACTIONS

Cyclosporine increases ambrisentan exposure; limit ambrisentan dose to 5 mg once daily (7).

8 USE IN SPECIFIC POPULATIONS

- Breastfeeding: Choose Letairis or breastfeeding (8.2).
- Not recommended in patients with moderate or severe hepatic impairment (8.7).

FULL PRESCRIBING INFORMATION

WARNING: EMBRYO-FETAL TOXICITY

Letairis is contraindicated for use during pregnancy because it may cause major birth defects if used by pregnant patients, based on studies in animals [see Contraindications (4.1), Warnings and Precautions (5.1), and Use in Specific Populations (8.1)].

Therefore, for females of reproductive potential, exclude pregnancy before the initiation of treatment with Letairis. Advise use of effective contraception before initiation, during treatment, and for one month after treatment with Letairis [see Dosage and Administration (2.2) Contraindications (4.1), Warnings and Precautions (5.1), and Use in Specific Populations (8.1, 8.3)]. When pregnancy is detected, discontinue Letairis as soon as possible (5.1).

1 INDICATIONS AND USAGE

Letairis is indicated for the treatment of pulmonary arterial hypertension (PAH) (WHO Group 1) in adult patients:

- To improve exercise ability and delay clinical worsening.
- In combination with tadalafil to reduce the risks of disease progression and hospitalization for worsening PAH, and to improve exercise ability [see Clinical Studies (14.2)].

Studies establishing effectiveness included predominantly patients with WHO Functional Class II–III symptoms and etiologies of idiopathic or heritable PAH (60%) or PAH associated with connective tissue diseases (34%).

2 DOSAGE AND ADMINISTRATION

2.1 Adult Dosage

Initiate treatment at 5 mg once daily, with or without tadalafil 20 mg once daily. At 4-week intervals, either the dose of Letairis or tadalafil can be increased, as needed and tolerated, to Letairis 10 mg or tadalafil 40 mg.

Do not split, crush, or chew tablets.

2.2 Pregnancy Testing in Females of Reproductive Potential

Exclude pregnancy before initiating treatment with Letairis in females of reproductive potential [see Warnings and Precautions (5.1), Use in Specific Populations (8.1, 8.3)].

3 DOSAGE FORMS AND STRENGTHS

5 mg and 10 mg film-coated tablets for oral administration

- Each 5 mg tablet is square convex, pale pink, with “5” on one side and “GSI” on the other side.
- Each 10 mg tablet is oval convex, deep pink, with “10” on one side and “GSI” on the other side.

4 CONTRAINDICATIONS

4.1 Pregnancy

Letairis may cause fetal harm when administered to a pregnant female. Letairis is contraindicated in females who are pregnant. Letairis was consistently shown to have teratogenic effects when administered to animals. If this drug is used during pregnancy, or if the patient becomes pregnant while taking this drug, the patient should be apprised of the potential hazard to a fetus [see Dosage and Administration (2.2), Warnings and Precautions (5.1), and Use in Specific Populations (8.1)].

4.2 Idiopathic Pulmonary Fibrosis

Letairis is contraindicated in patients with Idiopathic Pulmonary Fibrosis (IPF), including IPF patients with pulmonary hypertension (WHO Group 3) [see Clinical Studies (14.4)].

5 WARNINGS AND PRECAUTIONS

5.1 Embryo-fetal Toxicity

Based on data from animal reproduction studies, Letairis may cause fetal harm when administered during pregnancy and is contraindicated during pregnancy. The available human data for endothelin receptor antagonists do not establish the presence or absence of major birth defects related to the use of Letairis. Advise patients who can become pregnant of the potential risk to a fetus. Obtain a pregnancy test prior to initiation of treatment with Letairis. Advise patients who can become pregnant to use effective contraception prior to initiation of treatment, during treatment, and for one month after discontinuation of treatment with Letairis. When pregnancy is detected, discontinue use as soon as possible [see Dosage and Administration (2.2), and Use in Specific Populations (8.1, 8.3)].

5.2 Fluid Retention

Peripheral edema is a known class effect of endothelin receptor antagonists, and is also a clinical consequence of PAH and worsening PAH. In the placebo-controlled studies, there was an increased incidence of peripheral edema in patients treated with doses of 5 or 10 mg Letairis compared to placebo [see Adverse Reactions (6.1)]. Most edema was mild to moderate in severity.

In addition, there have been postmarketing reports of fluid retention in patients with pulmonary hypertension, occurring within weeks after starting Letairis. Patients required intervention with a diuretic, fluid management, or, in some cases, hospitalization for decompensating heart failure.

If clinically significant fluid retention develops, with or without associated weight gain, further evaluation should be undertaken to determine the cause, such as Letairis or underlying heart failure, and the possible need for specific treatment or discontinuation of Letairis therapy.

Peripheral edema/fluid retention is more common with Letairis plus tadalafil than with Letairis or tadalafil alone.

5.3 Pulmonary Edema with Pulmonary Veno-occlusive Disease (PVOD)

If patients develop acute pulmonary edema during initiation of therapy with vasodilating agents such as Letairis, the possibility of PVOD should be considered, and if confirmed Letairis should be discontinued.

5.4 Decreased Sperm Counts

Decreased sperm counts have been observed in human and animal studies with another endothelin receptor antagonist and in animal fertility studies with ambrisentan. Letairis may have an adverse effect on spermatogenesis. Counsel patients about potential effects on fertility [see Use in Specific Populations (8.6) and Nonclinical Toxicology (13.1)].

5.5 Hematological Changes

Decreases in hemoglobin concentration and hematocrit have followed administration of other endothelin receptor antagonists and were observed in clinical studies with Letairis. These decreases were observed within the first few weeks of treatment with Letairis, and stabilized thereafter. The mean decrease in hemoglobin from baseline to end of treatment for those patients receiving Letairis in the 12-week placebo-controlled studies was 0.8 g/dL.

Marked decreases in hemoglobin (>15% decrease from baseline resulting in a value below the lower limit of normal) were observed in 7% of all patients receiving Letairis (and 10% of patients receiving 10 mg) compared to 4% of patients receiving placebo. The cause of the decrease in hemoglobin is unknown, but it does not appear to result from hemorrhage or hemolysis.

In the long-term open-label extension of the two pivotal clinical studies, mean decreases from baseline (ranging from 0.9 to 1.2 g/dL) in hemoglobin concentrations persisted for up to 4 years of treatment.

There have been postmarketing reports of decreases in hemoglobin concentration and hematocrit that have resulted in anemia requiring transfusion.

Measure hemoglobin prior to initiation of Letairis, at one month, and periodically thereafter. Initiation of Letairis therapy is not recommended for patients with clinically significant anemia. If a clinically significant decrease in hemoglobin is observed and other causes have been excluded, consider discontinuing Letairis.

6 ADVERSE REACTIONS

Clinically significant adverse reactions that appear in other sections of the labeling include:

- Embryo-fetal Toxicity [see Warnings and Precautions (5.1), Use in Specific Populations (8.1)]
- Fluid Retention [see Warnings and Precautions (5.2)]
- Pulmonary Edema with PVOD [see Warnings and Precautions (5.3)]
- Decreased Sperm Count [see Warnings and Precautions (5.4)]
- Hematologic Changes [see Warnings and Precautions (5.5)]

6.1 Clinical Trials Experience

Because clinical trials are conducted under widely varying conditions, adverse reaction rates observed in the clinical trials of a drug cannot be directly compared to rates in the clinical trials of another drug and may not reflect the rates observed in practice.

Safety data for Letairis are presented from two 12-week, placebo-controlled studies (ARIES-1 and ARIES-2) in patients with pulmonary arterial hypertension (PAH), and one randomized, double-blind, active-controlled trial in 605 patients with PAH (AMBITION) comparing Letairis plus tadalafil to Letairis or tadalafil alone. The exposure to Letairis in these studies ranged from 1 day to 4 years (N=357 for at least 6 months and N=279 for at least 1 year).

In ARIES-1 and ARIES-2, a total of 261 patients received Letairis at doses of 2.5, 5, or 10 mg once daily and 132 patients received placebo. The adverse reactions that occurred in >3% more patients receiving Letairis than receiving placebo are shown in Table 1.

Table 1 Adverse Reactions with Placebo-Adjusted Rates >3% in ARIES-1 and ARIES-2
 | Placebo (N=132) | Letairis (N=261)
Adverse Reaction | n (%) | n (%) | Placebo-adjusted (%)
Peripheral edema | 14 (11) | 45 (17) | 6
Nasal congestion | 2 (2) | 15 (6) | 4
Sinusitis | 0 (0) | 8 (3) | 3
Flushing | 1 (1) | 10 (4) | 3

Most adverse drug reactions were mild to moderate and only nasal congestion was dose-dependent.

Few notable differences in the incidence of adverse reactions were observed for patients by age or sex. Peripheral edema was similar in younger patients (<65 years) receiving Letairis (14%; 29/205) or placebo (13%; 13/104), and was greater in elderly patients (≥65 years) receiving Letairis (29%; 16/56) compared to placebo (4%; 1/28). The results of such subgroup analyses must be interpreted cautiously.

The incidence of treatment discontinuations due to adverse events other than those related to PAH during the clinical trials in patients with PAH was similar for Letairis (2%; 5/261 patients) and placebo (2%; 3/132 patients). The incidence of patients with serious adverse events other than those related to PAH during the clinical trials in patients with PAH was similar for placebo (7%; 9/132 patients) and for Letairis (5%; 13/261 patients).

During 12-week controlled clinical trials, the incidence of aminotransferase elevations >3 × upper limit of normal (ULN) were 0% on Letairis and 2.3% on placebo. In practice, cases of hepatic injury should be carefully evaluated for cause.

Combination Use with Tadalafil

The mean exposure to Letairis + tadalafil in the AMBITION study was 78.7 weeks. The adverse reactions that occurred in >5% more patients receiving Letairis + tadalafil than receiving Letairis or tadalafil monotherapy in AMBITION are shown in Table 2.

Table 2 Adverse Reactions Reported More Commonly (>5%) on Letairis + Tadalafil than on Letairis or Tadalafil Monotherapy (ITT) in AMBITION
Adverse Reactions | Letairis + Tadalafil Combination Therapy (N=302) n (%) | Letairis Monotherapy (N=152) n (%) | Tadalafil Monotherapy (N=151) n (%)
Peripheral edema | 135 (45%) | 58 (38%) | 43 (28%)
Headache | 125 (41%) | 51 (34%) | 53 (35%)
Nasal congestion | 58 (19%) | 25 (16%) | 17 (11%)
Cough | 53 (18%) | 20 (13%) | 24 (16%)
Anemia | 44 (15%) | 11 (7%) | 17 (11%)
Dyspepsia | 32 (11%) | 5 (3%) | 18 (12%)
Bronchitis | 31 (10%) | 6 (4%) | 13 (9%)

Peripheral edema was more frequent on combination therapy; however, there was no notable difference observed in the incidence of peripheral edema in elderly patients (≥65 years) versus younger patients (<65 years) on combination therapy (44% vs. 45%) or Letairis monotherapy (37% vs. 39%) in AMBITION.

Treatment discontinuations due to adverse events while on randomized treatment were similar across treatment groups: 16% for Letairis + tadalafil, 14% for Letairis alone, and 13% for tadalafil alone.

Use in Patients with Prior Endothelin Receptor Antagonist (ERA) Related Serum Liver Enzyme Abnormalities

In an uncontrolled, open-label study, 36 patients who had previously discontinued endothelin receptor antagonists (ERAs: bosentan, an investigational drug, or both) due to aminotransferase elevations >3 × ULN were treated with Letairis. Prior elevations were predominantly moderate, with 64% of the ALT elevations <5 × ULN, but 9 patients had elevations >8 × ULN. Eight patients had been re-challenged with bosentan and/or the investigational ERA and all eight had a recurrence of aminotransferase abnormalities that required discontinuation of ERA therapy. All patients had to have normal aminotransferase levels on entry to this study. Twenty-five of the 36 patients were also receiving prostanoid and/or phosphodiesterase type 5 (PDE5) inhibitor therapy. Two patients discontinued early (including one of the patients with a prior 8 × ULN elevation). Of the remaining 34 patients, one patient experienced a mild aminotransferase elevation at 12 weeks on Letairis 5 mg that resolved with decreasing the dosage to 2.5 mg, and that did not recur with later escalations to 10 mg. With a median follow-up of 13 months and with 50% of patients increasing the dose of Letairis to 10 mg, no patients were discontinued for aminotransferase elevations. While the uncontrolled study design does not provide information about what would have occurred with re-administration of previously used ERAs or show that Letairis led to fewer aminotransferase elevations than would have been seen with those drugs, the study indicates that Letairis may be tried in patients who have experienced asymptomatic aminotransferase elevations on other ERAs after aminotransferase levels have returned to normal.

6.2 Postmarketing Experience

The following adverse reactions were identified during post-approval use of Letairis. Because these reactions were reported voluntarily from a population of uncertain size, it is not possible to estimate reliably the frequency or to establish a causal relationship to drug exposure: anemia requiring transfusion [see Warnings and Precautions (5.5)] heart failure (associated with fluid retention), symptomatic hypotension, and hypersensitivity (e.g., angioedema, rash).

Elevations of liver aminotransferases (ALT, AST) have been reported with Letairis use; in most cases alternative causes of the liver injury could be identified (heart failure, hepatic congestion, hepatitis, alcohol use, hepatotoxic medications). Other endothelin receptor antagonists have been associated with elevations of aminotransferases, hepatotoxicity, and cases of liver failure [see Adverse Reactions (6.1)].

7 DRUG INTERACTIONS

Multiple dose coadministration of ambrisentan and cyclosporine resulted in an approximately 2-fold increase in ambrisentan exposure in healthy volunteers; therefore, limit the dose of ambrisentan to 5 mg once daily when coadministered with cyclosporine [see Clinical Pharmacology (12.3)].

8 USE IN SPECIFIC POPULATIONS

8.1 Pregnancy

Risk Summary

Based on data from animal reproduction studies, Letairis may cause fetal harm, including birth defects and fetal death, when administered to a pregnant woman and is contraindicated during pregnancy. There are limited data on Letairis use in pregnant women. Available data from post-marketing reports and published literature over decades of use with endothelin receptor antagonists in the same class as Letairis have not identified an increased risk of major birth defects; however, these data are limited. Methodological limitations of these postmarketing reports and published literature include lack of a control group; limited information regarding dose, duration, and timing of drug exposure; and missing data. These limitations preclude establishing a reliable estimate of the risk of adverse fetal and neonatal outcomes with maternal endothelin receptor antagonist use. In animal reproduction studies, Letairis was teratogenic in rats and rabbits at doses which resulted in exposures of 3.5 and 1.7 times, respectively, the human dose of 10 mg per day [see Animal Data]. If this drug is used during pregnancy, or if the patient becomes pregnant while taking this drug, advise the patient of the potential hazard to a fetus [see Contraindications (4.1), Warnings and Precautions (5.1)].

The estimated background risk of major birth defects and miscarriage for the indicated population is unknown. All pregnancies have a background risk of birth defect, loss, or other adverse outcomes. In the U.S. general population, the estimated background risk of major birth defects and miscarriage in clinically recognized pregnancies is 2-4% and 15-20%, respectively.

Data

Animal Data

Letairis was teratogenic at oral dosages of ≥15 mg/kg/day (AUC 51.7 h•µg/mL) in rats and ≥7 mg/kg/day (24.7 h•µg/mL) in rabbits; it was not studied at lower dosages. These dosages are of 3.5 and 1.7 times, respectively, the human dose of 10 mg per day (14.8 h•µg/mL) based on AUC. In both species, there were abnormalities of the lower jaw and hard and soft palate, malformation of the heart and great vessels, and failure of formation of the thymus and thyroid.

A preclinical study in rats has shown decreased survival of newborn pups (mid and high dosages) and effects on testicle size and fertility of pups (high dosage) following maternal treatment with ambrisentan from late gestation through weaning. The mid and high dosages were 51 ×, and 170 × (on a mg/m^2 body surface area basis) the maximum oral human dose of 10 mg and an average adult body weight of 70 kg. These effects were absent at a maternal dosage 17 × the human dose based on mg/m^2.

8.2 Lactation

Risk Summary

It is not known whether ambrisentan is present in human milk. Because many drugs are present in human milk and because of the potential for serious adverse reactions in breastfed infants from Letairis, a decision should be made whether to discontinue breastfeeding or discontinue Letairis, taking into account the importance of the drug to the mother.

8.3 Females and Males of Reproductive Potential

Based on data from animal reproductive toxicity studies, ambrisentan may cause fetal harm, including birth defects and fetal death, when administered to a pregnant patient and is contraindicated during pregnancy [see Contraindications (4.1), Use in Specific Populations (8.1)].

Pregnancy Testing

Verify that patients who can become pregnant are not pregnant prior to initiating ambrisentan. The patient should contact their physician immediately for pregnancy testing if onset of menses is delayed or pregnancy is suspected. If the pregnancy test is positive, the physician and patient should discuss the risks to the pregnancy and the fetus.

Contraception

Patients who can become pregnant who are using ambrisentan should use effective contraception prior to initiation of treatment, during treatment, and for one month after discontinuation of treatment with ambrisentan to prevent pregnancy [see Warnings and Precautions (5.1)].

Infertility

Males

In a 6-month study of another endothelin receptor antagonist, bosentan, 25 male patients with WHO functional class III and IV PAH and normal baseline sperm count were evaluated for effects on testicular function. There was a decline in sperm count of at least 50% in 25% of the patients after 3 or 6 months of treatment with bosentan. One patient developed marked oligospermia at 3 months, and the sperm count remained low with 2 follow-up measurements over the subsequent 6 weeks.

Bosentan was discontinued and after 2 months the sperm count had returned to baseline levels. In 22 patients who completed 6 months of treatment, sperm count remained within the normal range and no changes in sperm morphology, sperm motility, or hormone levels were observed. Based on these findings and preclinical data [see Nonclinical Toxicology (13.1)] from endothelin receptor antagonists, it cannot be excluded that endothelin receptor antagonists such as Letairis have an adverse effect on spermatogenesis. Counsel patients about the potential effects on fertility [see Warnings and Precautions (5.5)].

8.4 Pediatric Use

Safety and effectiveness of Letairis in pediatric patients have not been established.

Juvenile Animal Data

In juvenile rats administered ambrisentan orally once daily during postnatal day 7 to 26, 36, or 62, a decrease in brain weight (−3% to −8%) with no morphologic or neurobehavioral changes occurred after breathing sounds, apnea, and hypoxia were observed, at exposures approximately 1.8 to 7.0 times human pediatric exposures at 10 mg, based on AUC.

8.5 Geriatric Use

In the two placebo-controlled clinical studies of Letairis, 21% of patients were ≥65 years old and 5% were ≥75 years old. The elderly (age ≥65 years) showed less improvement in walk distances with Letairis than younger patients did, but the results of such subgroup analyses must be interpreted cautiously. Peripheral edema was more common in the elderly than in younger patients.

8.6 Renal Impairment

The impact of renal impairment on the pharmacokinetics of ambrisentan has been examined using a population pharmacokinetic approach in PAH patients with creatinine clearances ranging between 20 and 150 mL/min. There was no significant impact of mild or moderate renal impairment on exposure to ambrisentan [see Clinical Pharmacology (12.3)]. Dose adjustment of Letairis in patients with mild or moderate renal impairment is therefore not required. There is no information on the exposure to ambrisentan in patients with severe renal impairment.

The impact of hemodialysis on the disposition of ambrisentan has not been investigated.

8.7 Hepatic Impairment

Pre-existing Hepatic Impairment

The influence of pre-existing hepatic impairment on the pharmacokinetics of ambrisentan has not been evaluated. Because there is in vitro and in vivo evidence of significant metabolic and biliary contribution to the elimination of ambrisentan, hepatic impairment might be expected to have significant effects on the pharmacokinetics of ambrisentan [see Clinical Pharmacology (12.3)]. Letairis is not recommended in patients with moderate or severe hepatic impairment. There is no information on the use of Letairis in patients with mild pre-existing impaired liver function; however, exposure to ambrisentan may be increased in these patients.

Elevation of Liver Transaminases

Other endothelin receptor antagonists (ERAs) have been associated with aminotransferase (AST, ALT) elevations, hepatotoxicity, and cases of liver failure [see Adverse Reactions (6.1, 6.2)]. In patients who develop hepatic impairment after Letairis initiation, the cause of liver injury should be fully investigated. Discontinue Letairis if elevations of liver aminotransferases are >5 × ULN or if elevations are accompanied by bilirubin >2 × ULN, or by signs or symptoms of liver dysfunction and other causes are excluded.

10 OVERDOSAGE

There is no experience with overdosage of Letairis. The highest single dose of Letairis administered to healthy volunteers was 100 mg, and the highest daily dose administered to patients with PAH was 10 mg once daily. In healthy volunteers, single doses of 50 mg and 100 mg (5 to 10 times the maximum recommended dose) were associated with headache, flushing, dizziness, nausea, and nasal congestion. Massive overdosage could potentially result in hypotension that may require intervention.

11 DESCRIPTION

Letairis contains ambrisentan, an endothelin receptor antagonist. The chemical name of ambrisentan is (+)-(2S)-2-[(4,6-dimethylpyrimidin-2-yl)oxy]-3-methoxy-3,3-diphenylpropanoic acid. It has a molecular formula of C22H22N2O4 and a molecular weight of 378.42 and has the following structural formula:

Figure 1 Ambrisentan Structural Formula

Ambrisentan is a white to off-white, crystalline solid. It is a carboxylic acid with a pKa of 4.0. Ambrisentan is practically insoluble in water and in aqueous solutions at low pH. Solubility increases in aqueous solutions at higher pH. In the solid state ambrisentan is very stable, is not hygroscopic, and is not light sensitive.

Letairis is available as 5 mg and 10 mg film-coated tablets for once daily oral administration. The tablets include the following inactive ingredients: croscarmellose sodium, lactose monohydrate, magnesium stearate and microcrystalline cellulose. The tablets are film-coated with a coating material containing FD&C Red #40 aluminum lake, lecithin, polyethylene glycol, polyvinyl alcohol, talc, and titanium dioxide. Each square, pale pink Letairis tablet contains 5 mg of ambrisentan. Each oval, deep pink Letairis tablet contains 10 mg of ambrisentan. Letairis tablets are unscored.

12 CLINICAL PHARMACOLOGY

12.1 Mechanism of Action

Endothelin-1 (ET-1) is a potent autocrine and paracrine peptide. Two receptor subtypes, ETA and ETB, mediate the effects of ET-1 in the vascular smooth muscle and endothelium. The primary actions of ETA are vasoconstriction and cell proliferation, while the predominant actions of ETB are vasodilation, antiproliferation, and ET-1 clearance.

In patients with PAH, plasma ET-1 concentrations are increased as much as 10-fold and correlate with increased mean right atrial pressure and disease severity. ET-1 and ET-1 mRNA concentrations are increased as much as 9-fold in the lung tissue of patients with PAH, primarily in the endothelium of pulmonary arteries. These findings suggest that ET-1 may play a critical role in the pathogenesis and progression of PAH.

Ambrisentan is a high-affinity (Ki=0.011 nM) ETA receptor antagonist with a high selectivity for the ETA versus ETB receptor (>4000-fold). The clinical impact of high selectivity for ETA is not known.

12.2 Pharmacodynamics

Cardiac Electrophysiology

In a randomized, positive- and placebo-controlled, parallel-group study, healthy subjects received either Letairis 10 mg daily followed by a single dose of 40 mg, placebo followed by a single dose of moxifloxacin 400 mg, or placebo alone. Letairis 10 mg daily had no significant effect on the QTc interval. The 40 mg dose of Letairis increased mean QTc at tmax by 5 ms with an upper 95% confidence limit of 9 ms. For patients receiving Letairis 5–10 mg daily and not taking metabolic inhibitors, no significant QT prolongation is expected.

N-terminal pro-B-type natriuretic peptide (NT-proBNP)

In AMBITION [see Clinical Studies (14.2)], the decrease in NT-proBNP in patients on Letairis plus tadalafil was observed early (Week 4) and was sustained, with a reduction of 63% on Letairis plus tadalafil, 50% on Letairis alone, and 41% on tadalafil alone at Week 24.

12.3 Pharmacokinetics

The pharmacokinetics of ambrisentan (S-ambrisentan) in healthy subjects is dose proportional. The absolute bioavailability of ambrisentan is not known. Ambrisentan is absorbed with peak concentrations occurring approximately 2 hours after oral administration in healthy subjects and PAH patients. Food does not affect its bioavailability. In vitro studies indicate that ambrisentan is a substrate of P-gp. Ambrisentan is highly bound to plasma proteins (99%). The elimination of ambrisentan is predominantly by non-renal pathways, but the relative contributions of metabolism and biliary elimination have not been well characterized. In plasma, the AUC of 4-hydroxymethyl ambrisentan accounts for approximately 4% relative to parent ambrisentan AUC. The in vivo inversion of S-ambrisentan to R-ambrisentan is negligible. The mean oral clearance of ambrisentan is 38 mL/min and 19 mL/min in healthy subjects and in PAH patients, respectively. Although ambrisentan has a 15-hour terminal half-life, the mean trough concentration of ambrisentan at steady-state is about 15% of the mean peak concentration and the accumulation factor is about 1.2 after long-term daily dosing, indicating that the effective half-life of ambrisentan is about 9 hours.

Drug Interactions

In Vitro Studies

Studies with human liver tissue indicate that ambrisentan is metabolized by CYP3A, CYP2C19, and uridine 5'-diphosphate glucuronosyltransferases (UGTs) 1A9S, 2B7S, and 1A3S. In vitro studies suggest that ambrisentan is a substrate of the Organic Anion Transporting Polypeptides OATP1B1 and OATP1B3, and P-glycoprotein (P-gp). Drug interactions might be expected because of these factors; however, a clinically relevant interaction has been demonstrated only with cyclosporine [see Drug Interactions (7)]. In vitro studies found ambrisentan to have little to no inhibition of human hepatic transporters. Ambrisentan demonstrated weak dose-dependent inhibition of OATP1B1, OATP1B3, and NTCP (IC50 of 47 µM, 45 µM, and approximately 100 µM, respectively) and no transporter-specific inhibition of BSEP, BRCP, P-gp, or MRP2. Ambrisentan does not inhibit or induce drug metabolizing enzymes at clinically relevant concentrations.

In Vivo Studies

The effects of other drugs on ambrisentan pharmacokinetics and the effects of ambrisentan on the exposure to other drugs are shown in Figure 2 and Figure 3, respectively.

Figure 2 Effects of Other Drugs on Ambrisentan Pharmacokinetics

* Omeprazole: based on population pharmacokinetic analysis in PAH patients

** Rifampin: AUC and Cmax were measured at steady-state. On Day 3 of coadministration a transient 2-fold increase in AUC was noted that was no longer evident by Day 7. Day 7 results are presented.

Figure 3 Effects of Ambrisentan on Other Drugs

* Active metabolite of mycophenolate mofetil

** GMR (95% CI) for INR

13 NONCLINICAL TOXICOLOGY

13.1 Carcinogenesis, Mutagenesis, Impairment of Fertility

Oral carcinogenicity studies of up to two years duration were conducted at starting doses of 10, 30, and 60 mg/kg/day in rats (8 to 48 times the maximum recommended human dose [MRHD] on a mg/m^2 basis) and at 50, 150, and 250 mg/kg/day in mice (28 to 140 times the MRHD). In the rat study, the high- and mid-dose male and female groups had their doses lowered to 40 and 20 mg/kg/day, respectively, in week 51 because of effects on survival. The high-dose males and females were taken off drug completely in weeks 69 and 93, respectively. The only evidence of ambrisentan-related carcinogenicity was a positive trend in male rats, for the combined incidence of benign basal cell tumor and basal cell carcinoma of skin/subcutis in the mid-dose group (high-dose group excluded from analysis), and the occurrence of mammary fibroadenomas in males in the high-dose group. In the mouse study, high-dose male and female groups had their doses lowered to 150 mg/kg/day in week 39 and were taken off drug completely in week 96 (males) or week 76 (females). In mice, ambrisentan was not associated with excess tumors in any dosed group.

Positive findings of clastogenicity were detected, at drug concentrations producing moderate to high toxicity, in the chromosome aberration assay in cultured human lymphocytes. There was no evidence for genetic toxicity of ambrisentan when tested in vitro in bacteria (Ames test) or in vivo in rats (micronucleus assay, unscheduled DNA synthesis assay).

The development of testicular tubular atrophy and impaired fertility has been linked to the chronic administration of endothelin receptor antagonists in rodents. Testicular tubular degeneration was observed in rats treated with ambrisentan for two years at doses ≥10 mg/kg/day (8-fold MRHD). Increased incidences of testicular findings were also observed in mice treated for two years at doses ≥50 mg/kg/day (28-fold MRHD). Effects on sperm count, sperm morphology, mating performance, and fertility were observed in fertility studies in which male rats were treated with ambrisentan at oral doses of 300 mg/kg/day (236-fold MRHD). At doses of ≥10 mg/kg/day, observations of testicular histopathology in the absence of fertility and sperm effects were also present.

14 CLINICAL STUDIES

14.1 Pulmonary Arterial Hypertension (PAH)

Two 12-week, randomized, double-blind, placebo-controlled, multicenter studies were conducted in 393 patients with PAH (WHO Group 1). The two studies were identical in design except for the doses of Letairis and the geographic region of the investigational sites. ARIES-1 compared once-daily doses of 5 mg and 10 mg Letairis to placebo, while ARIES-2 compared once-daily doses of 2.5 mg and 5 mg Letairis to placebo. In both studies, Letairis or placebo was added to current therapy, which could have included a combination of anticoagulants, diuretics, calcium channel blockers, or digoxin, but not epoprostenol, treprostinil, iloprost, bosentan, or sildenafil. The primary study endpoint was 6-minute walk distance. In addition, clinical worsening, WHO functional class, dyspnea, and SF-36® Health Survey were assessed.

Patients had idiopathic or heritable PAH (64%) or PAH associated with connective tissue diseases (32%), HIV infection (3%), or anorexigen use (1%). There were no patients with PAH associated with congenital heart disease.

Patients had WHO functional class I (2%), II (38%), III (55%), or IV (5%) symptoms at baseline. The mean age of patients was 50 years, 79% of patients were female, and 77% were Caucasian.

Submaximal Exercise Ability

Results of the 6-minute walk distance at 12 weeks for the ARIES-1 and ARIES-2 studies are shown in Table 3 and Figure 4.

Table 3 Changes from Baseline in 6-Minute Walk Distance (meters) (ARIES-1 and ARIES-2)
 | ARIES-1 |  |  | ARIES-2
 | Placebo (N=67) | 5 mg (N=67) | 10 mg (N=67) | Placebo (N=65) | 2.5 mg (N=64) | 5 mg (N=63)
Baseline | 342 ± 73 | 340 ± 77 | 342 ± 78 | 343 ± 86 | 347 ± 84 | 355 ± 84
Mean change from baseline | -8 ± 79 | 23 ± 83 | 44 ± 63 | -10 ± 94 | 22 ± 83 | 49 ± 75
Placebo-adjusted mean change from baseline | _ | 31 | 51 | _ | 32 | 59
Placebo-adjusted median change from baseline | _ | 27 | 39 | _ | 30 | 45
p-value [p-values are Wilcoxon rank sum test comparisons of Letairis to placebo at Week 12 stratified by idiopathic or heritable PAH and non-idiopathic, non-heritable PAH patients] | _ | 0.008 | <0.001 | _ | 0.022 | <0.001
Mean ± standard deviation

Figure 4 Mean Change in 6-Minute Walk Distance (ARIES-1 and ARIES-2)

Mean change from baseline in 6-minute walk distance in the placebo and Letairis groups.
Values are expressed as mean ± standard error of the mean.

In both studies, treatment with Letairis resulted in a significant improvement in 6-minute walk distance for each dose of Letairis and the improvements increased with dose. An increase in 6-minute walk distance was observed after 4 weeks of treatment with Letairis, with a dose-response observed after 12 weeks of treatment. Improvements in walk distance with Letairis were smaller for elderly patients (age ≥65) than younger patients and for patients with secondary PAH than for patients with idiopathic or heritable PAH. The results of such subgroup analyses must be interpreted cautiously.

Clinical Worsening

Time to clinical worsening of PAH was defined as the first occurrence of death, lung transplantation, hospitalization for PAH, atrial septostomy, study withdrawal due to the addition of other PAH therapeutic agents, or study withdrawal due to early escape. Early escape was defined as meeting two or more of the following criteria: a 20% decrease in the 6-minute walk distance; an increase in WHO functional class; worsening right ventricular failure; rapidly progressing cardiogenic, hepatic, or renal failure; or refractory systolic hypotension. The clinical worsening events during the 12-week treatment period of the Letairis clinical trials are shown in Table 4 and Figure 5.

Table 4 Time to Clinical Worsening (ARIES-1 and ARIES-2)
 | ARIES-1 |  | ARIES-2
 | Placebo (N=67) | Letairis (N=134) | Placebo (N=65) | Letairis (N=127)
Clinical worsening, no. (%) | 7 (10%) | 4 (3%) | 13 (22%) | 8 (6%)
Hazard ratio | _ | 0.28 | _ | 0.30
p-value, Log-rank test | _ | 0.030 | _ | 0.005
Intention-to-treat population.
Note: Patients may have had more than one reason for clinical worsening.
Nominal p-values

There was a significant delay in the time to clinical worsening for patients receiving Letairis compared to placebo. Results in subgroups such as the elderly were also favorable.

Figure 5 Time to Clinical Worsening (ARIES-1 and ARIES-2)

Time from randomization to clinical worsening with Kaplan-Meier estimates of the proportions of patients without events in ARIES-1 and ARIES-2.

p-values shown are the log-rank comparisons of Letairis to placebo stratified by idiopathic or heritable PAH and non-idiopathic, non-heritable PAH patients.

14.2 Combination Treatment of PAH

In a randomized, double-blind, active-controlled trial (AMBITION), 605 patients with WHO Functional Class II or III PAH were randomized 2:1:1 to once daily Letairis plus tadalafil or to Letairis or tadalafil alone. Treatment was initiated with Letairis 5 mg and tadalafil 20 mg. If tolerated, tadalafil was increased to 40 mg at 4 weeks and Letairis was increased to 10 mg at 8 weeks.

The primary endpoint was time to first occurrence of (a) death, (b) hospitalization for worsening PAH, (c) >15% decrease from baseline in 6MWD combined with WHO Functional Class III or IV symptoms sustained over 14 days (short term clinical worsening), or (d) reduction in 6MWD sustained over 14 days combined with WHO Functional Class III or IV symptoms sustained over 6 months (inadequate long term clinical response).

Patients had idiopathic PAH (55%), heritable PAH (3%), or PAH associated with connective tissue diseases, congenital heart disease, stable HIV infection, or drugs or toxins (APAH, 43%). Median time from diagnosis to first study drug administration was 25 days. Approximately 32% and 68% of patients were in WHO Functional Class II and III, respectively. The mean patient age was 55.7 years (34% were ≥65 years old). Most patients were white (90%) and female (76%); 45% were North American.

Principal results are shown in Figures 6 and 7.

Figure 6 Time to Primary Endpoint Event (AMBITION)

Figure 7 Primary Endpoint Events and First Occurrences of Each Component at Any Time (AMBITION)

The treatment effect of Letairis plus tadalafil compared with individual monotherapy on time to first primary endpoint event was consistent across subgroups. (Figure 8).

Figure 8 Primary Endpoint by Subgroups (AMBITION)

Note: The figure above presents effects in various subgroups all of which are baseline characteristics and all of which were pre-specified, if not the groupings. The 95% confidence limits that are shown do not take into account how many comparisons were made, nor do they reflect the effect of a particular factor after adjustment for all other factors. Apparent homogeneity or heterogeneity among groups should not be over interpreted.

Exercise Ability

Results of the 6MWD at 24 weeks for the AMBITION study are shown in Table 5 and Figure 9.

Table 5 6-Minute Walk Distance at Week 24 (meters) [Missing values at Week 24 were imputed using Worst Rank scores for patients with an adjudicated clinical failure event of death or hospitalization, and Last Observed Carried Forward otherwise.] (AMBITION)
 | Letairis + Tadalafil (N=302) | Letairis Monotherapy (N=152) | Tadalafil Monotherapy (N=151)
Baseline (median) | 356 | 366 | 352
Change from baseline (median) | 43 | 23 | 22
Median difference from Letairis + Tadalafil (95% CI) |  | 24 (11, 37) | 20 (8, 32)
P-Value |  | 0.0004 | 0.0016

Figure 9 Median Change in 6-Minute Walk Distance (meters) in AMBITION

14.3 Long-term Treatment of PAH

In long-term follow-up of patients who were treated with Letairis (2.5 mg, 5 mg, or 10 mg once daily) in the two pivotal studies and their open-label extension (N=383), Kaplan-Meier estimates of survival at 1, 2, and 3 years were 93%, 85%, and 79%, respectively. Of the patients who remained on Letairis for up to 3 years, the majority received no other treatment for PAH. These uncontrolled observations do not allow comparison with a group not given Letairis and cannot be used to determine the long-term effect of Letairis on mortality.

14.4 Adverse Effects in Idiopathic Pulmonary Fibrosis (IPF)

A randomized controlled study in patients with IPF, with or without pulmonary hypertension (WHO Group 3), compared Letairis (N=329) to placebo (N=163). The study was terminated after 34 weeks for lack of efficacy, and was found to demonstrate a greater risk of disease progression or death on Letairis. More patients taking Letairis died (8% vs. 4%), had a respiratory hospitalization (13% vs. 6%), and had a decrease in FVC/DLCO (17% vs. 12%) [see Contraindications (4.2)].

16 HOW SUPPLIED/STORAGE AND HANDLING

Letairis film-coated tablets are supplied as follows:

Tablet Strength | Package Configuration | NDC No. | Description of Tablet; Debossed on Tablet; Size
5 mg | 30 count blister | 61958-0801-2 | Square convex; pale pink; "5" on side 1 and "GSI" on side 2; 6.6 mm Square
5 mg | 30 count bottle | 61958-0801-1 | Square convex; pale pink; "5" on side 1 and "GSI" on side 2; 6.6 mm Square
5 mg | 10 count blister | 61958-0801-3 | Square convex; pale pink; "5" on side 1 and "GSI" on side 2; 6.6 mm Square
5 mg | 10 count bottle | 61958-0801-5 | Square convex; pale pink; "5" on side 1 and "GSI" on side 2; 6.6 mm Square
10 mg | 30 count blister | 61958-0802-2 | Oval convex; deep pink; "10" on side 1 and "GSI" on side 2; 9.8 mm × 4.9 mm Oval
10 mg | 30 count bottle | 61958-0802-1 | Oval convex; deep pink; "10" on side 1 and "GSI" on side 2; 9.8 mm × 4.9 mm Oval
10 mg | 10 count blister | 61958-0802-3 | Oval convex; deep pink; "10" on side 1 and "GSI" on side 2; 9.8 mm × 4.9 mm Oval
10 mg | 10 count bottle | 61958-0802-5 | Oval convex; deep pink; "10" on side 1 and "GSI" on side 2; 9.8 mm × 4.9 mm Oval

STORAGE AND HANDLING

Store at 25° C (77° F); excursions permitted to 15–30° C (59–86° F) [see USP controlled room temperature]. Store Letairis in its original packaging.

17 PATIENT COUNSELING INFORMATION

Advise patients to read the FDA-approved patient labeling (Medication Guide).

Embryo-fetal Toxicity

Instruct patients on the risk of fetal harm when Letairis is used in pregnancy [see Warnings and Precautions (5.1) and Use in Specific Populations (8.1)]. Instruct females of reproductive potential to immediately contact their physician if they suspect they may be pregnant.

Educate and counsel patients who can become pregnant about the need to use effective contraception prior to treatment with Letairis, during treatment, and for one month after treatment discontinuation [see Warnings and Precautions (5.1) and Use in Specific Populations (8.1, 8.3)]. Patients who can become pregnant should have a negative pregnancy test prior to treatment with Letairis [see Dosage and Administration (2.2), Contraindications (4.1), Warnings and Precautions (5.1), Use in Specific Populations (8.1, 8.3)].

Counsel patients who can become pregnant about pregnancy planning and prevention, including emergency contraception, or designate counseling by another healthcare provider trained in contraceptive counseling [see Boxed Warning].

Hepatic Effects

Advise patients of the symptoms of potential liver injury and instruct them to report any of these symptoms to their physician.

Hematological Change

Advise patients of the importance of hemoglobin testing.

Other Risks Associated with Letairis

Instruct patients that the risks associated with Letairis also include the following:

- Decreases in sperm count
- Fluid overload

Administration

Advise patients not to split, crush, or chew tablets.

Gilead Sciences, Inc., Foster City, CA 94404

Letairis is a registered trademark of Gilead Sciences, Inc. Gilead and the Gilead logo are trademarks of Gilead Sciences, Inc. Other brands noted herein are the property of their respective owners.

© 2025 Gilead Sciences, Inc.

GS22-081-018

Medication Guide
Letairis® (le-TAIR-is)
(ambrisentan) tablets

Read this Medication Guide before you start taking Letairis and each time you get a refill. There may be new information. This Medication Guide does not take the place of talking with your doctor about your medical condition or your treatment.

What is the most important information I should know about Letairis?

- Serious birth defects.
  Letairis can cause serious birth defects if taken during pregnancy.
  - Females should not be pregnant when they start taking Letairis or become pregnant during treatment with Letairis.
  - Females who are able to get pregnant should have a negative pregnancy test before beginning treatment with Letairis. Talk to your doctor about your menstrual cycle. Your doctor will decide when to do a pregnancy test, and will order a pregnancy test for you depending on your menstrual cycle.
    - Females who are able to get pregnant are females who:
      - have entered puberty, even if they have not started their menstrual period, and
      - have a uterus, and
      - have not gone through menopause. Menopause means that you have not had a menstrual period for at least 12 months for natural reasons, or that you have had your ovaries removed.
    - Females who are not able to get pregnant are females who:
      - have not yet entered puberty, or
      - do not have a uterus, or
      - have gone through menopause. Menopause means that you have not had a menstrual period for at least 12 months for natural reasons, or that you have had your ovaries removed, or
      - who are infertile for any other medical reason and this infertility is permanent and cannot be reversed
  Females who are able to get pregnant should use effective contraception before beginning Letairis, during treatment with Letairis, and for one month after stopping Letairis because the medicine may still be in the body.
  - Talk with your doctor or gynecologist (a doctor who specializes in female reproduction) to find out about options for acceptable forms of birth control that you may use to prevent pregnancy during treatment with Letairis.
  - If you decide that you want to change the form of birth control that you use, talk with your doctor or gynecologist to be sure that you choose another acceptable form of birth control.
  - Do not have unprotected sex. Talk to your doctor or pharmacist right away if you have unprotected sex or if you think your birth control has failed. Your doctor may tell you to use emergency birth control.
  - Tell your doctor right away if you miss a menstrual period or think you may be pregnant for any reason.

If you are the parent or caregiver of a female child who started taking Letairis before reaching puberty, you should check your child regularly to see if she is developing signs of puberty. Tell your doctor right away if you notice that she is developing breast buds or pubic hair. Your doctor should decide if your child has reached puberty. Your child may reach puberty before having her first menstrual period.

What is Letairis?

- Letairis is a prescription medicine used to treat pulmonary arterial hypertension (PAH), which is high blood pressure in the arteries of your lungs.
- Letairis can improve your ability to exercise and it can help slow down the worsening of your physical condition and symptoms.
- When taken with tadalafil, Letairis is used to reduce the risk of your disease progressing, to reduce the risk of hospitalization due to worsening pulmonary arterial hypertension (PAH), and to improve your ability to exercise.
- It is not known if Letairis is safe and effective in children.

Who should not take Letairis?
Do not take Letairis if:

- you are pregnant, plan to become pregnant, or become pregnant during treatment with Letairis. Letairis can cause serious birth defects. (See “What is the most important information I should know about Letairis?”)
- you have a condition called Idiopathic Pulmonary Fibrosis (IPF)

What should I tell my doctor before taking Letairis?
Before you take Letairis, tell your doctor if you:

- have been told that you have a low red blood cell level (anemia)
- have liver problems
- have any other medical conditions

Tell your doctor about all the medicines you take, including prescription and over-the-counter medicines, vitamins, and herbal supplements. Letairis and other medicines may affect each other, causing side effects. Do not start any new medicines until you check with your doctor.
Especially tell your doctor if you take the medicine cyclosporine (Gengraf, Neoral, Sandimmune). Your doctor may need to change your dose of Letairis.

How should I take Letairis?

- Take Letairis exactly as your doctor tells you to take it. Do not stop taking Letairis unless your doctor tells you to stop.
- You can take Letairis with or without food.
- Do not split, crush or chew Letairis tablets.
- It will be easier to remember to take Letairis if you take it at the same time each day.
- If you take more than your regular dose of Letairis, call your doctor right away.
- If you miss a dose, take it as soon as you remember that day. Take your next dose at the regular time. Do not take two doses at the same time to make up for a missed dose.

What should I avoid while taking Letairis?

- Do not get pregnant while taking Letairis. (See the serious birth defects section of the Medication Guide above called “What is the most important information I should know about Letairis?”) If you miss a menstrual period, or think you might be pregnant, call your doctor right away.
- It is not known if Letairis passes into your breast milk. You should not breastfeed if you are taking Letairis. Talk to your doctor about the best way to feed your baby if you take Letairis.

What are the possible side effects of Letairis?
Letairis can cause serious side effects including:

- See “What is the most important information I should know about Letairis?”
- Swelling all over the body (fluid retention) can happen within weeks after starting Letairis. Tell your doctor right away if you have any unusual weight gain, tiredness, or trouble breathing while taking Letairis. These may be symptoms of a serious health problem. You may need to be treated with medicine or need to go to the hospital.
- Decreased sperm count. Decreased sperm counts have happened in some men taking a medicine that is like Letairis. A decreased sperm count may affect the ability to father a child. Tell your doctor if being able to have children is important to you.
- Low red blood cell levels (anemia) can happen during the first weeks after starting Letairis. If this happens, you may need a blood transfusion. Your doctor will do blood tests to check your red blood cells before starting Letairis. Your doctor may also do these tests during treatment with Letairis.

The most common side effects of Letairis include:

- swelling of hands, legs, ankles and feet (peripheral edema)
- stuffy nose (nasal congestion)

- inflamed nasal passages (sinusitis)
- hot flashes or getting red in the face (flushing)

Some medicines that are like Letairis can cause liver problems. Tell your doctor if you get any of these symptoms of a liver problem while taking Letairis:

- loss of appetite
- nausea or vomiting
- fever
- achiness

- generally do not feel well
- pain in the upper right stomach (abdominal) area
- yellowing of your skin or the whites of your eyes
- dark urine
- itching

Tell your doctor if you have any side effect that bothers you or that does not go away. These are not all of the possible side effects of Letairis. For more information, ask your doctor or pharmacist.
Call your doctor for medical advice about side effects. You may report side effects to FDA at 1-800-FDA-1088.

How should I store Letairis?
Store Letairis at room temperature between 68°F to 77°F (20°C to 25°C), in the package it comes in.
Keep Letairis and all medicines out of the reach of children.

General information about the safe and effective use of Letairis
Medicines are sometimes prescribed for purposes other than those listed in a Medication Guide. Do not use Letairis for a condition for which it was not prescribed. Do not give Letairis to other people, even if they have the same symptoms that you have. It may harm them.
This Medication Guide summarizes the most important information about Letairis. If you would like more information, ask your doctor. You can ask your doctor or pharmacist for information about Letairis that is written for health professionals.

What are the ingredients in Letairis?
Active ingredient: ambrisentan
Inactive Ingredients: croscarmellose sodium, lactose monohydrate, magnesium stearate and microcrystalline cellulose. The tablets are film-coated with a coating material containing FD&C Red #40 aluminum lake, lecithin, polyethylene glycol, polyvinyl alcohol, talc, and titanium dioxide.
Gilead Sciences, Inc., Foster City, CA 94404
Letairis is a registered trademark of Gilead Sciences, Inc. Gilead and the Gilead logo are trademarks of Gilead Sciences, Inc. Other brands noted herein are the property of their respective owners.
© 2025 Gilead Sciences, Inc.
GS22-081-018
For more information call 1-866-664-5327 or go to www.letairis.com or www.gilead.com.

This Medication Guide has been approved by the U.S. Food and Drug Administration.

Revised April 2025

PRINCIPAL DISPLAY PANEL - 5 mg Tablet Carton

NDC 61958- 0801-3

Letairis®
(ambrisentan) Tablets, 5 mg

Rx only

Each tablet contains 5 mg of ambrisentan.

10 tablets

Note to Authorized Dispenser: Provide a copy of the Letairis Medication
Guide included in this carton to each patient.

GILEAD

PRINCIPAL DISPLAY PANEL - 10 mg Tablet Carton

NDC 61958- 0802-3

Letairis®
(ambrisentan) Tablets, 10 mg

Rx only

Each tablet contains 10 mg of ambrisentan.

10 tablets

Note to Authorized Dispenser: Provide a copy of the Letairis Medication
Guide included in this carton to each patient.

GILEAD